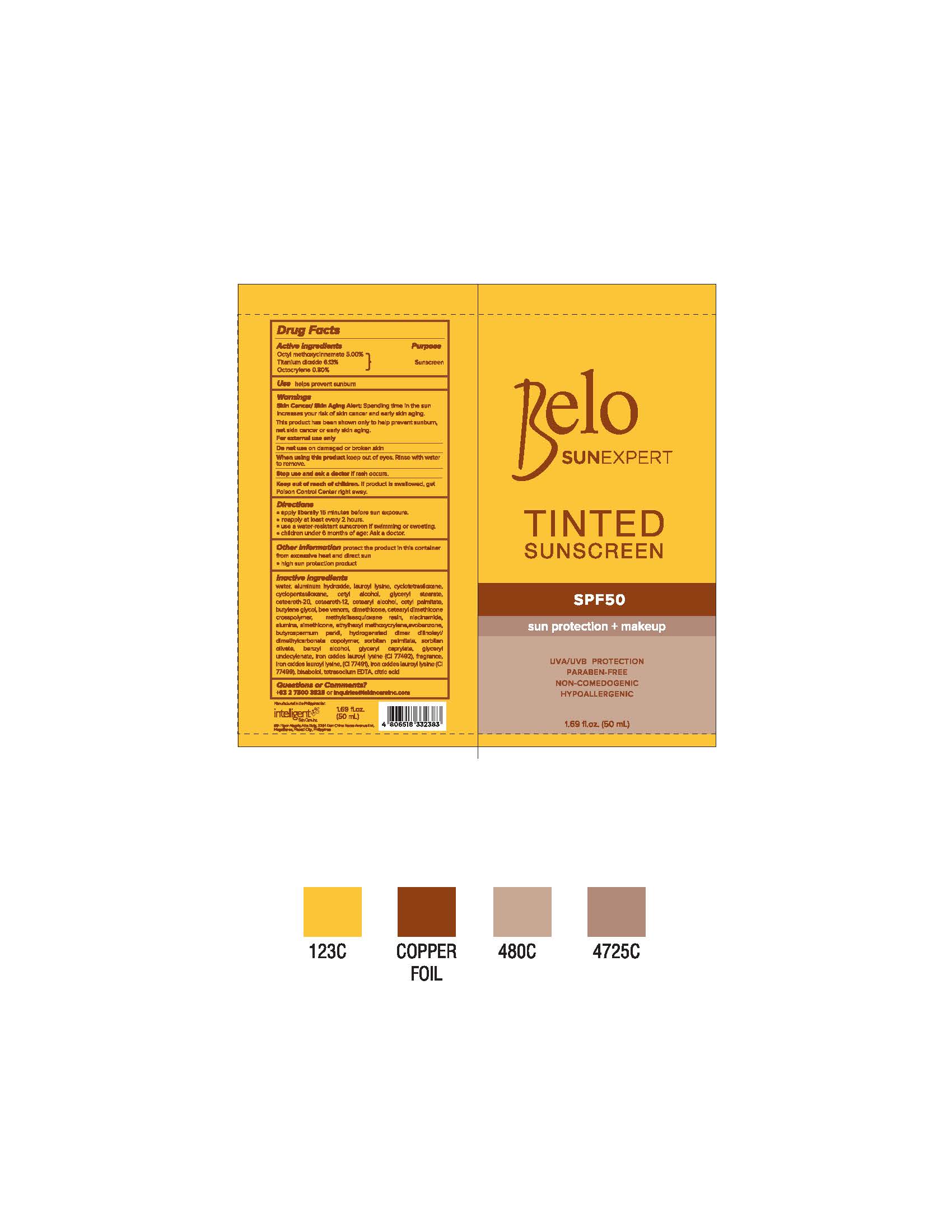 DRUG LABEL: Belo Sun Expert Tinted Sunscreen
NDC: 82701-001 | Form: CREAM
Manufacturer: Intelligent Skin Care Inc.
Category: otc | Type: HUMAN OTC DRUG LABEL
Date: 20221129

ACTIVE INGREDIENTS: TITANIUM DIOXIDE 3.065 mg/50 mg; OCTOCRYLENE 0.4 mg/50 mg; OCTINOXATE 2.5 mg/50 mg
INACTIVE INGREDIENTS: APIS MELLIFERA VENOM; BUTYROSPERMUM PARKII (SHEA) BUTTER UNSAPONIFIABLES; NIACINAMIDE; GLYCERYL CAPRYLATE; WATER; ALUMINUM OXIDE; BENZYL ALCOHOL; CYCLOMETHICONE 5; LAUROYL LYSINE; POLYMETHYLSILSESQUIOXANE/TRIMETHYLSILOXYSILICATE; FERROSOFERRIC OXIDE; LEVOMENOL; CETOSTEARYL ALCOHOL; DIMETHICONE; BUTYLENE GLYCOL; GLYCERYL 1-UNDECYLENATE; FERRIC OXIDE YELLOW; ALUMINUM HYDROXIDE; ETHYLHEXYL METHOXYCRYLENE; CETYL ALCOHOL; C30-45 ALKYL CETEARYL DIMETHICONE CROSSPOLYMER; SILICON DIOXIDE; AVOBENZONE; CITRIC ACID MONOHYDRATE; CETEARETH-12; CETYL PALMITATE; GLYCERYL MONOSTEARATE; FERRIC OXIDE RED; EDETATE SODIUM; PEG-80 SORBITAN PALMITATE; CYCLOMETHICONE 4; POLYOXYL 20 CETOSTEARYL ETHER

Intelligent Skin Belo private labeled

Active Ingredients

Active Ingredients Purpose

Octyl methoxycinnamate 5% Sunscreen

Titanium dioxide 6.13%

Octocrylene .8%

Use

helps prevent sunburn

Warnings

Skin Cancer/Skin Aging Alert: Spending time in the sun increases your risk of skin cancer and early skin aging. This product has been shown only to help prevent sunburn, not skin cancer or early skin aging.

For external use only

Do not use on damaged or broken skin

When using this product keep out of eyes. Rinse with water to remove.

Stop use and ask a doctor if rash occurs.

Keep out of reach of children. If product is swallowed, get Poison Control Center right away.

Directions

- apply liberally 15 minutes before sun exposure.
- reapply at least every 2 hours.
- use a water-resistant sunscreen if swimming or sweating.
- children under 6 months of age: Ask a doctor.

Other Information

protect the product in this container from excessive heat and direct sun

- high sun protection product

Inactive Ingredients

water, aluminum hydroxide, lauroyl lysine, cyclotetrasiloxane, cyclopentasiloxane, cetyl alcohol, glyceryl stearate, ceteareth-20, ceteraeth-12, cetearyl alcohol, cetyl palmitate, butylene glycol, bee venom, dimethicone, cetearyl dimethicone crosspolymer, methylsisesquioxane resin, niacinamide, alumina, simethicone, ethylhexyl methoxycrylene, avobenzone, butyrospermum parkii, hydrogenated dimer dilinoleyl/dimethylcarbonate copolymer, sorbitan palmitate, sorbitan olivate, benzyl alcohol, glyceryl caprylate, glyceryl undecylenate, iron oxides lauroyl lysine (CI 77492), fragrance, iron oxides lauroyl lysine (CI 66491), iron oxides lauroyl lysine (CI 77499) bisabolol, tetrasodium EDTA, citric acid

Questions or Comments?

+63 2 7500 3825 or inquiries@iskincareinc.com

Purpose

Helps prevent sunburn